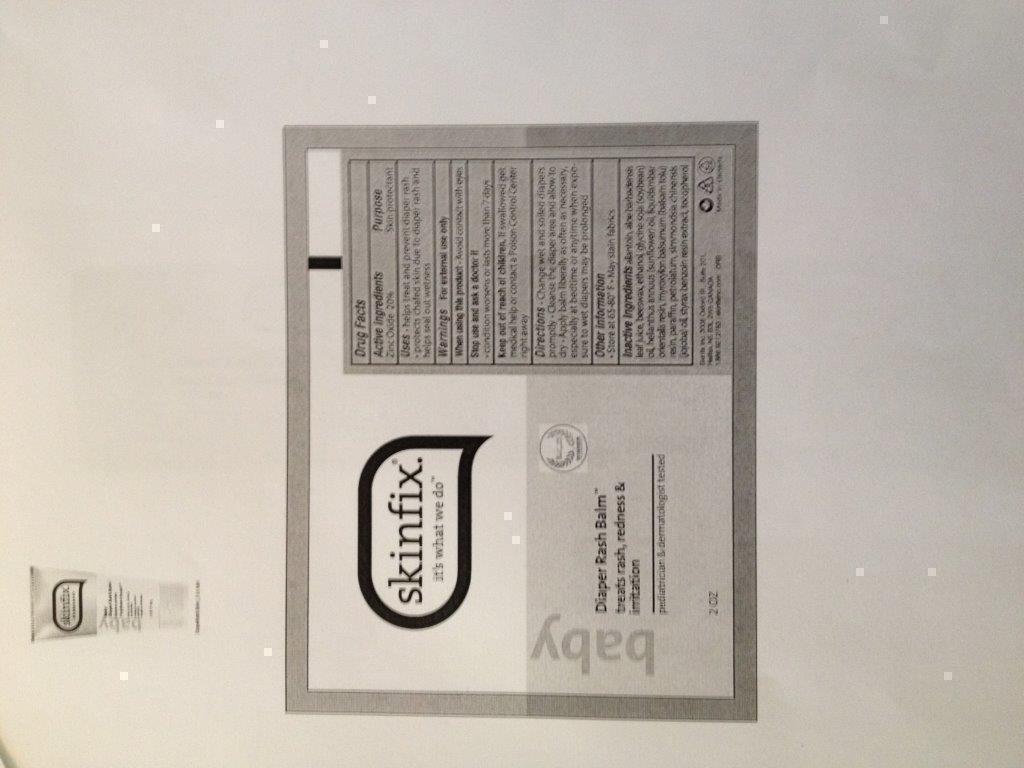 DRUG LABEL: Diaper Rash Balm
NDC: 61328-001 | Form: OINTMENT
Manufacturer: Skinfix, Inc.
Category: otc | Type: HUMAN OTC DRUG LABEL
Date: 20131209

ACTIVE INGREDIENTS: ZINC OXIDE 0.2 g/1 g
INACTIVE INGREDIENTS: PETROLATUM; ALCOHOL; SOYBEAN OIL; SUNFLOWER OIL; JOJOBA OIL; WHITE WAX; PARAFFIN; ALLANTOIN; BENZOIN RESIN; LIQUIDAMBAR ORIENTALIS RESIN; TOLU BALSAM; ALOE

Diaper Rash Balm

Package Label Principal Display

Treats rash, redness & Irritation

Uses - helps treat and prevent diaper rash. protects chafed skin due to diaper rash and helps seal out wetness.

Warnings - For external use only

When using this product . Avoid contact with eyes

Keep out of reach of children. If swallowed get medical help or contact a Poison Control Center right away

Directions - Change wet and soiled diapers promptly. Cleanse the diaper area and allow to dry. Apply balm liberally as often as necessary, especially at bedtime or anytime when exposure to wet diapers may be prolonged.